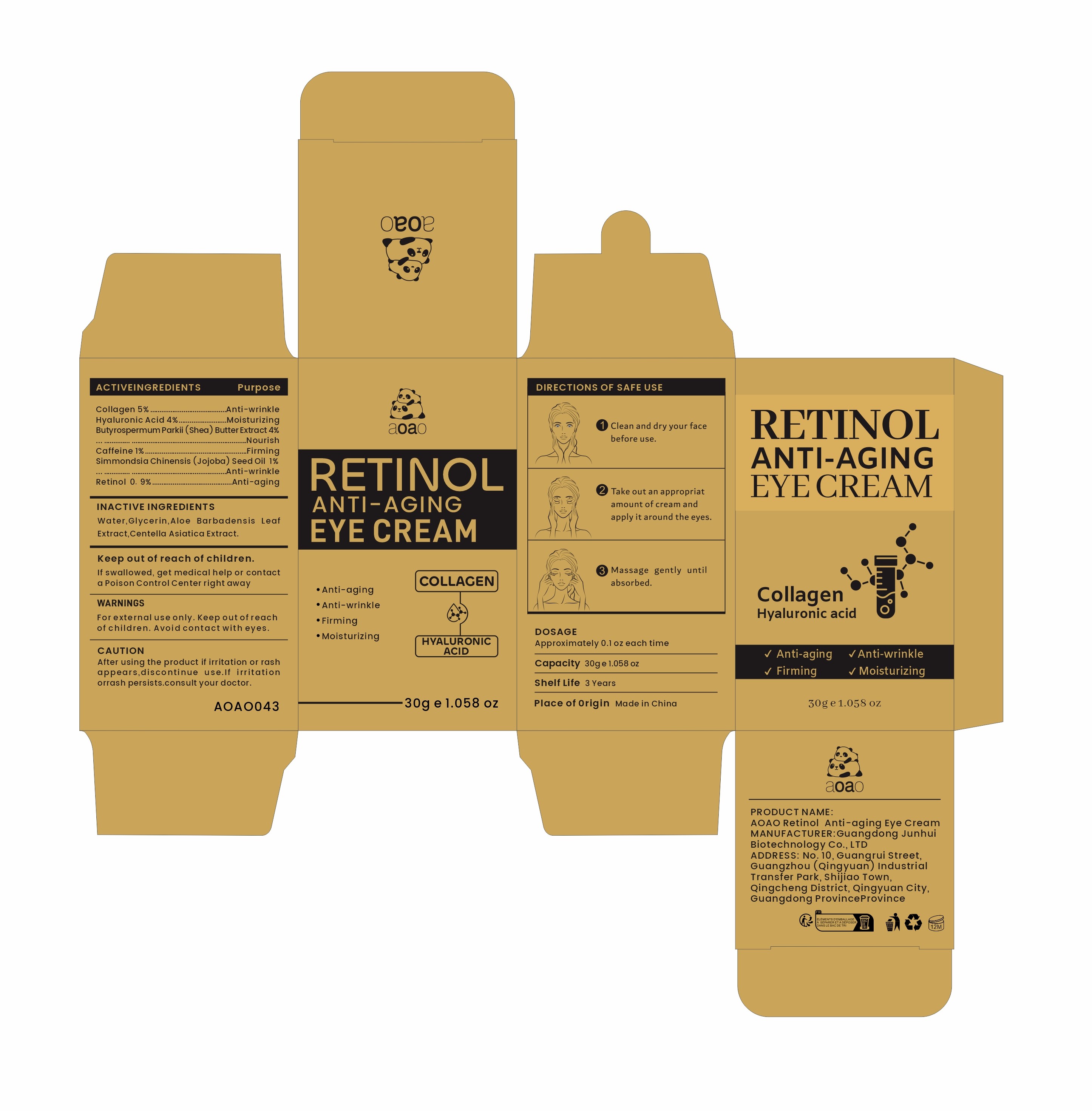 DRUG LABEL: AOAO Retinol Anti-aging Eye Cream
NDC: 84509-042 | Form: CREAM
Manufacturer: Guangdong Junhui Biotechnology Co., LTD
Category: otc | Type: HUMAN OTC DRUG LABEL
Date: 20241106

ACTIVE INGREDIENTS: HYALURONIC ACID 1200 mg/30 g; COLLAGEN, SOLUBLE, FISH SKIN 1500 mg/30 g; SIMMONDSIA CHINENSIS (JOJOBA) SEED OIL 300 mg/30 g; BUTYROSPERMUM PARKII (SHEA) BUTTER EXTRACT 1200 mg/30 g; RETINOL 270 mg/30 g; CAFFEINE 300 mg/30 g
INACTIVE INGREDIENTS: GLYCERIN; CENTELLA ASIATICA TRITERPENOIDS; WATER; ALOE BARBADENSIS LEAF EXTRACT

Active Ingredients

Collagen 5%
Butyrospermum Parkii (Shea) Butter Extract 4%
Hyaluronic Acid 4%
Caffeine 1%
Simmondsia Chinensis (Jojoba) Seed Oil 1%
Retinol 0.9%

Purpose

Anti-wrinkle
Nourish
Moisturizing
Firming
Anti-aging

Uses

1、After cleansing use the Rice andCeramide Moisturizing Toner toprep the skin
2、Apply the Rice and CeramideMoisturizing Emulsion tomoisturize the skin
3、Use the Rice & CeramideMoisturizing Cream to plump andsoften the skin

Warnings

For external use only. Keep out ofreach of children.Avoid contact with eyes

Keep out of reach of children

If swallowed, get medical help or contact a Poison Control Center right away

CAUTION

After using the product if irritation or rash appears,discontinue use.If irritation or
rash persists.consult your doctor.

DOSAGE

Approximately 0.1oz each time

Product Name

AOAO Retinol Anti-aging Eye Cream

Inactive Ingredients

Water,Glycerin，Aloe Barbadensis Leaf Extract，Centella Asiatica Extract

Manufacturer

Guangdong Junhui Biotechnology Co., LTD

ADDRESS

No. 10, Guangrui Street, Guangzhou (Qingyuan) Industrial Transfer Park, Shijiao Town, Qingcheng District, Qingyuan City, Guangdong Province

Capacity

30g e1.058 oz

Shelf Life

3 Years

DESCRIPTION

Made in China